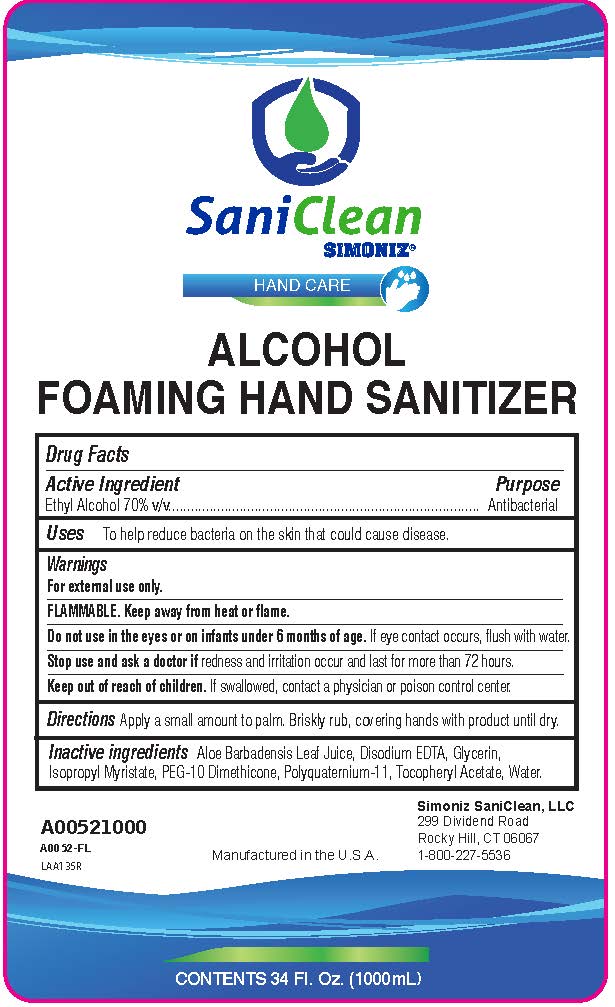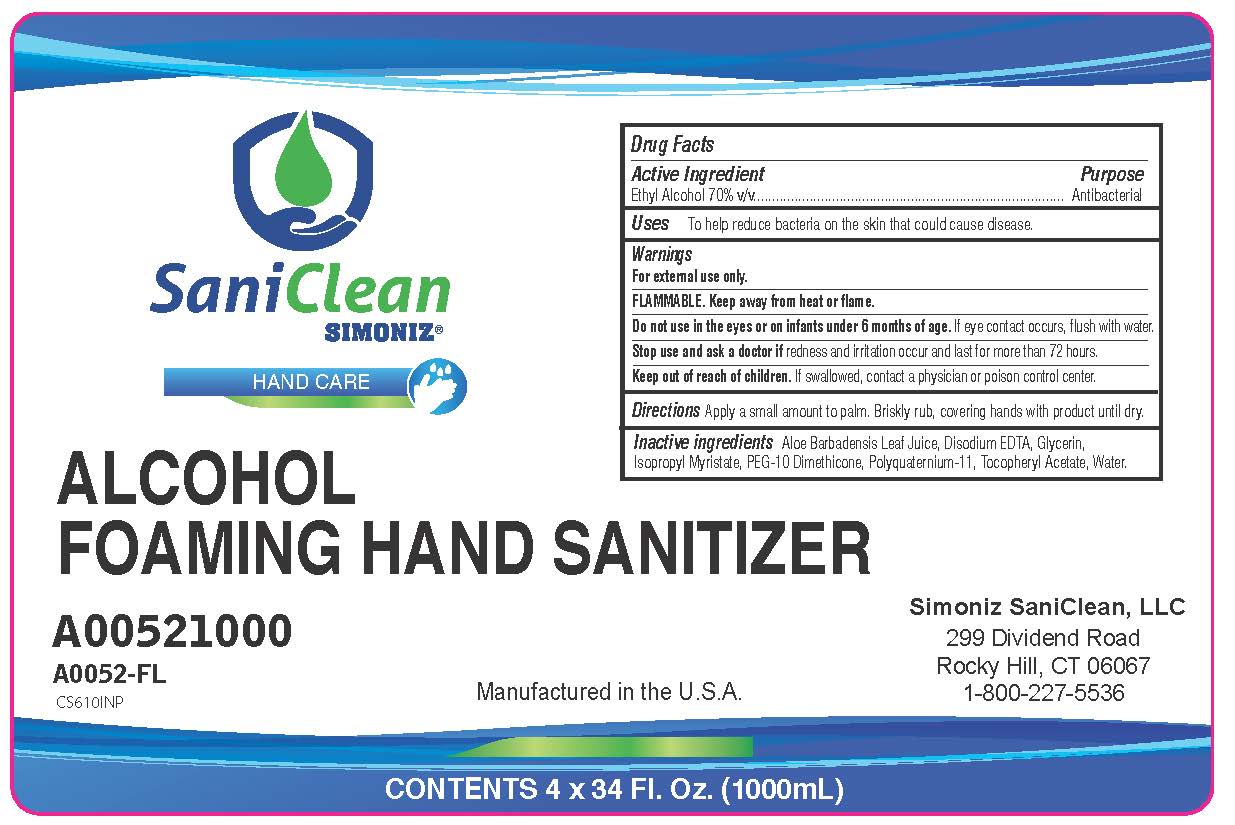 DRUG LABEL: Saniclean
NDC: 63900-150 | Form: LIQUID
Manufacturer: Simoniz Saniclean, LLC
Category: otc | Type: HUMAN OTC DRUG LABEL
Date: 20251027

ACTIVE INGREDIENTS: ALCOHOL 70 g/100 mL
INACTIVE INGREDIENTS: EDETATE DISODIUM; GLYCERIN; ALOE BARBADENSIS LEAF; WATER; PEG-10 DIMETHICONE (600 CST); POLYQUATERNIUM-11 (1000000 MW); .ALPHA.-TOCOPHEROL ACETATE, DL-; ISOPROPYL MYRISTATE

Foaming Hand Sanitizer with 70% Ethyl Alcohol

Active Ingredients

Ethyl Alcohol 70% v/v

Purpose

Antibacterial

Uses

To help reduce bacteria on the skin that could cause disease.

Warnings

For external use only

FLAMMABLE. Keep Away from heat or flame.

Do not use in the eyes or on infants under 6 months of age. If eye contact occurs, flush with water.

Stop use and ask a doctor if redness and irritation occurs and last for more than 72 hours.

KEEP OUT OF REACH OF CHILDREN

Keep out of the reach of childeren. If swallowed, contact a physician or poison control center.

DOSAGE AND ADMINISTRATION

Directions Apply a small amount to palm. Briskly rub, covering hands with product until dry.

INACTIVE INGREDIENT

Inactive ingredients Aloe Barbadensis Leaf Juice, Disodium EDTA, Glycerin, Isopropyl Myristate, PEG-10 Dimethicone, Polyquaternium-11, Tocopheryl Acetate, Water

Simoniz Saniclean, LLC

299 Dividend Road

Rocky Hill, CT 06067

1-800-227-5536

PACKAGE LABEL

Saniclean

Simoniz

Hand Care

Alcohol

Foaming Hand Sanitizer

Manufactured in the U.S.A.

Contents 34 F;. Oz. (1000mL)